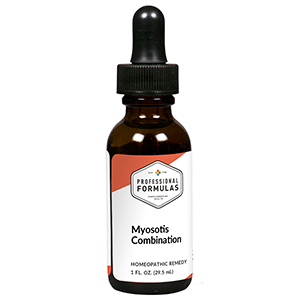 DRUG LABEL: Myosotis Combination
NDC: 63083-9234 | Form: LIQUID
Manufacturer: Professional Complementary Health Formulas
Category: homeopathic | Type: HUMAN OTC DRUG LABEL
Date: 20190815

ACTIVE INGREDIENTS: SCROPHULARIA NODOSA WHOLE 3 [hp_X]/29.5 mL; TEUCRIUM SCORODONIA FLOWERING TOP 3 [hp_X]/29.5 mL; VERONICA BECCABUNGA WHOLE 3 [hp_X]/29.5 mL; EQUISETUM HYEMALE WHOLE 4 [hp_X]/29.5 mL; FUMARIA OFFICINALIS FLOWERING TOP 4 [hp_X]/29.5 mL; GERANIUM ROBERTIANUM WHOLE 4 [hp_X]/29.5 mL; MYOSOTIS ARVENSIS WHOLE 4 [hp_X]/29.5 mL; NASTURTIUM OFFICINALE 4 [hp_X]/29.5 mL; SODIUM SULFATE 4 [hp_X]/29.5 mL; PINUS SYLVESTRIS LEAFY TWIG 4 [hp_X]/29.5 mL; GENTIANA LUTEA ROOT 5 [hp_X]/29.5 mL; ENGLISH WALNUT 6 [hp_X]/29.5 mL; SMILAX ORNATA ROOT 6 [hp_X]/29.5 mL; ARANEUS DIADEMATUS 9 [hp_X]/29.5 mL; ANHYDROUS DIBASIC CALCIUM PHOSPHATE 12 [hp_X]/29.5 mL; FERROUS IODIDE 12 [hp_X]/29.5 mL; BOS TAURUS LYMPH VESSEL 12 [hp_X]/29.5 mL; THYROID, UNSPECIFIED 12 [hp_X]/29.5 mL
INACTIVE INGREDIENTS: ALCOHOL; WATER

R234

ACTIVE INGREDIENTS

Scrophularia nodosa 3X
Teucrium scorodonia 3X
Veronica beccabunga 3X
Equisetum hyemale 4X
Fumaria officinalis 4X
Geranium robertianum 4X
Myosotis arvensis 4X
Nasturtium aquaticum 4X
Natrum sulphuricum 4X
Pinus sylvestris 4X
Gentiana lutea 5X
Juglans regia 6X
Sarsaparilla 6X
Aranea diadema 9X
Calcarea phosphorica 12X
Ferrum iodatum 12X
Lymph 12X
Thyroid 12X

QUESTIONS

Professional Formulas

PO Box 2034 Lake Oswego, OR 97035

INDICATIONS

For the temporary relief of cough, bronchial congestion, minor sore throat, fatigue, or malaise.*

PURPOSE

*Claims based on traditional homeopathic practice, not accepted medical evidence. Not FDA evaluated.

WARNINGS

If symptoms do not improve or are accompanied by a fever, consult a doctor. Keep out of the reach of children. In case of overdose, get medical help or contact a poison control center right away. If pregnant or breastfeeding, ask a healthcare professional before use.

Keep out of the reach of children.

PREGNANCY OR BREAST FEEDING

If pregnant or breastfeeding, ask a healthcare professional before use.

DIRECTIONS

Place drops under tongue 30 minutes before/after meals. Adults and children 12 years and over: Take 10 drops up to 3 times per day. Consult a physician for use in children under 12 years of age.

OTHER INFORMATION

Tamper resistant. If seal is broken, do not use. After opening, close container tightly and store at room temperature away from heat.

INACTIVE INGREDIENTS

40% ethanol, purified water.

LABEL

Est 1985

Professional Formulas

Complementary Health

Myosotis Combination

Homeopathic Remedy

1 FL. OZ. (29.5 mL)